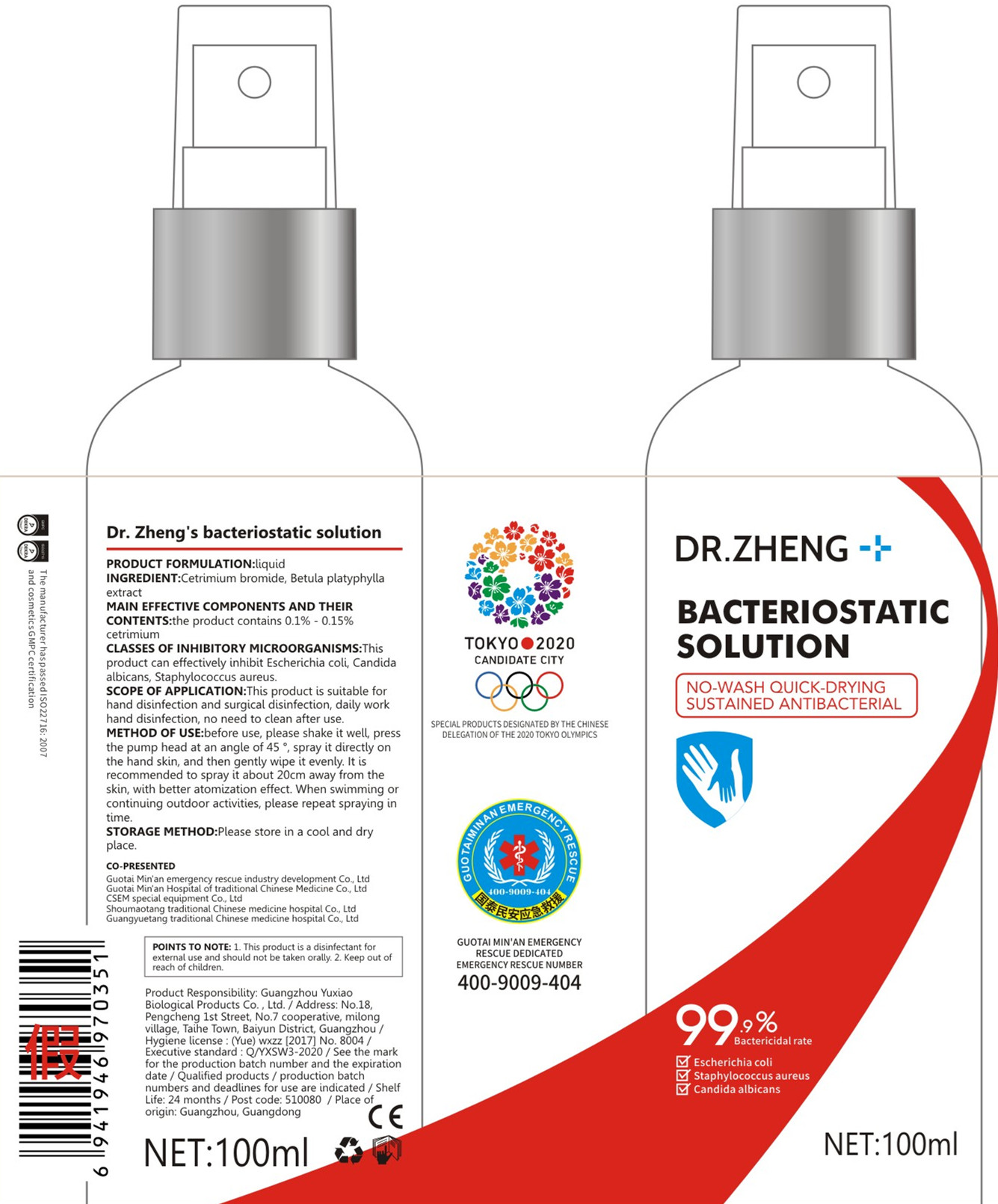 DRUG LABEL: Dr. Zheng bacteriostatic solution
NDC: 42091-001 | Form: LIQUID
Manufacturer: Guangzhou Yuxiao Biological Products Co., Ltd
Category: otc | Type: HUMAN OTC DRUG LABEL
Date: 20200411

ACTIVE INGREDIENTS: CETRIMONIUM BROMIDE 0.125 mg/100 mL
INACTIVE INGREDIENTS: BETULA PLATYPHYLLA BARK; PHELLODENDRON AMURENSE BARK

DOSAGE AND ADMINISTRATION

Please store in a cool and dry place.

INACTIVE INGREDIENT

Phellodendron extract

Betula platyphylla extract

INDICATIONS AND USAGE

before use, please shake it well, press the pump head at an angle of 45 : spray it directly on the hand skin, and then gently wipe it evenly. It is recommended to spray it about 20cm away from the skin, with better atomization effect. When swimming or continuing outdoor activities, please repeat spraying in time.

ACTIVE INGREDIENT

CETRIMONIUM BROMIDE

keep out of children

PURPOSE

Disinfection
Sterilization

WARNINGS

1. This product is a disinfectant for external use and should not be taken orally.
2. Keep out of reach of children.